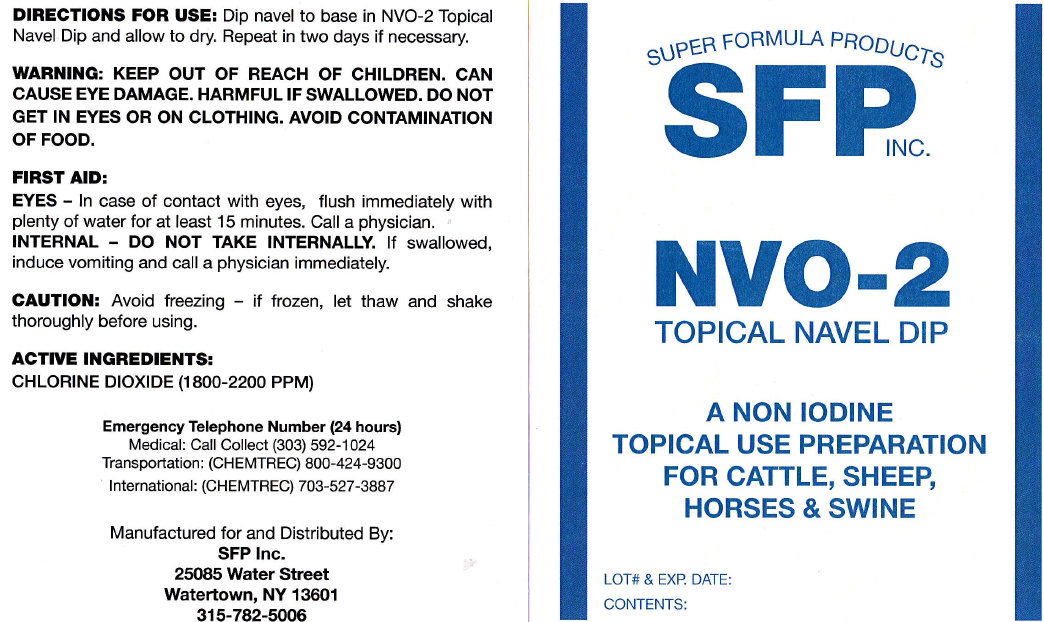 DRUG LABEL: SFP INC. NVO-2 TOPICAL NAVEL DIP
NDC: 35723-103 | Form: LIQUID
Manufacturer: SUPER FORMULA PRODUCTS INC.
Category: animal | Type: OTC ANIMAL DRUG LABEL
Date: 20140723

ACTIVE INGREDIENTS: CHLORINE DIOXIDE 2200 mg/1 L

SFP INC. NVO-2 TOPICAL NAVEL DIP

DIRECTIONS FOR USE:

Dip navel to base in NVO-2 Topical Navel Dip and allow to dry. Repeat in two days if necessary.

WARNING: KEEP OUT OF REACH OF CHILDREN. CAN CAUSE EYE DAMAGE. HARMFUL IF SWALLOWED. DO NOT GET IN EYES OR ON CLOTHING. AVOID CONTAMINATION OF FOOD.

FIRST AID:
EYES - In case of contact with eyes, flush immediately with plenty of water for at least 15 minutes. Call a physician.
INTERNAL - DO NOT TAKE INTERNALLY. If swallowed, induce vomiting and call a physician immediately.
CAUTION: Avoid freezing - if frozen, let thaw and shake thoroughly before using.

ACTIVE INGREDIENTS:

CHLORINE DIOXIDE (1800-2200 PPM)